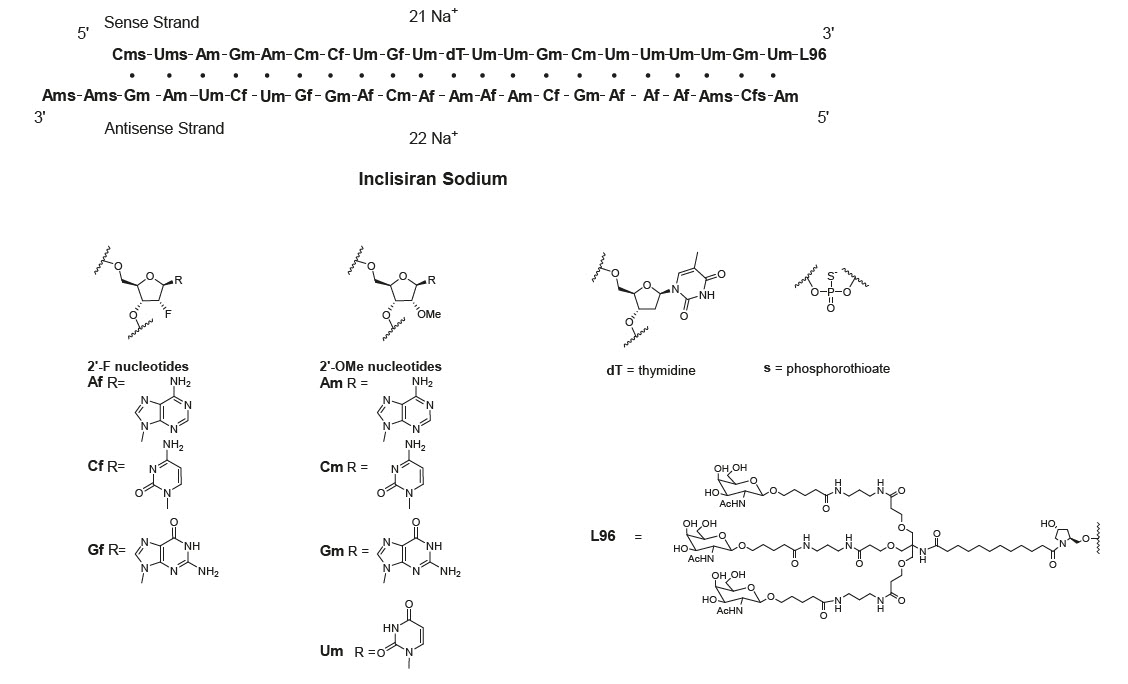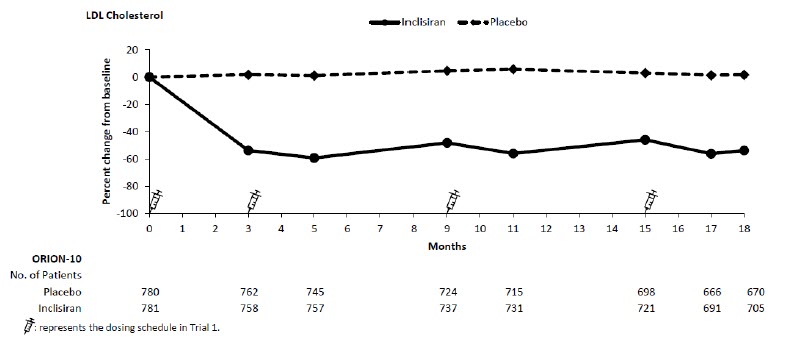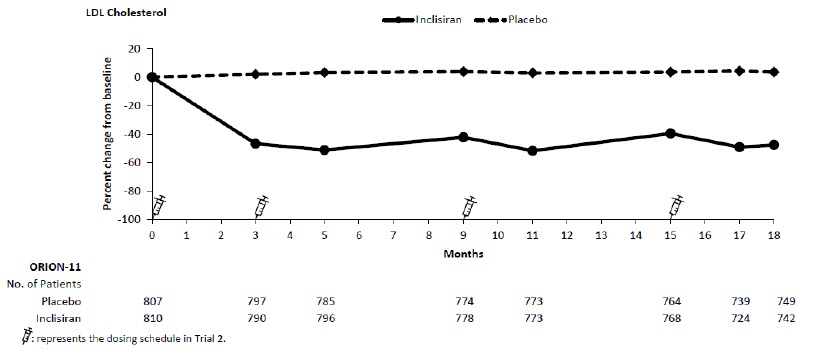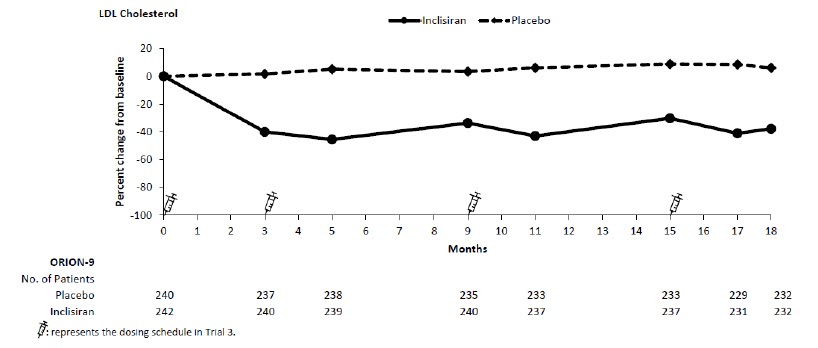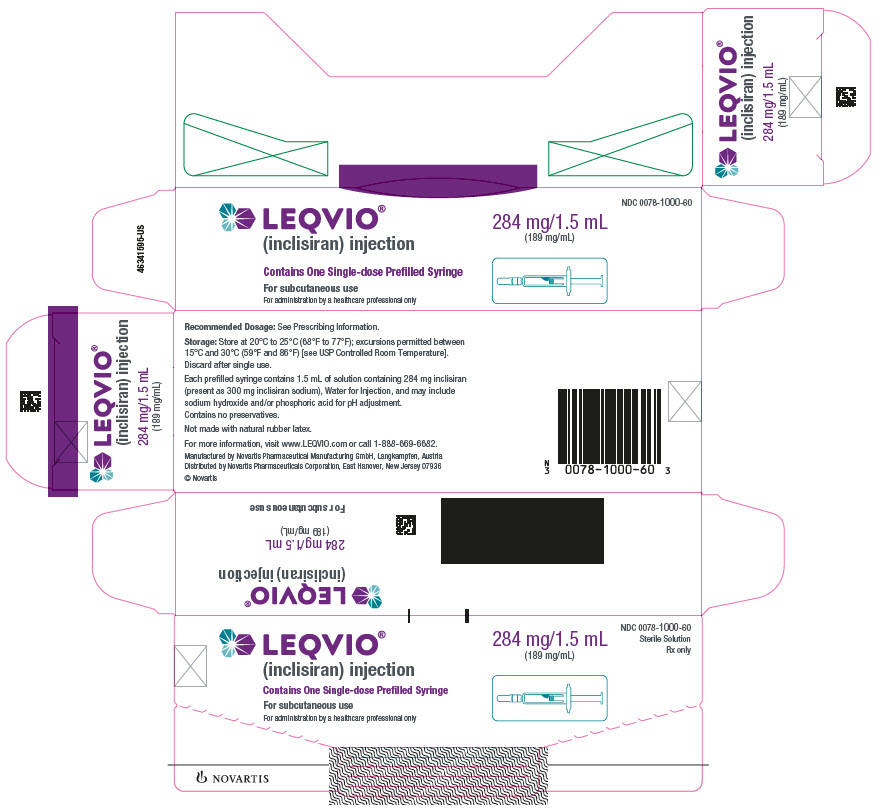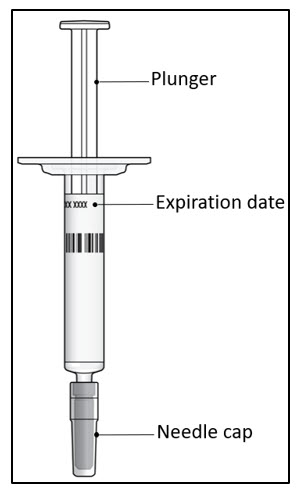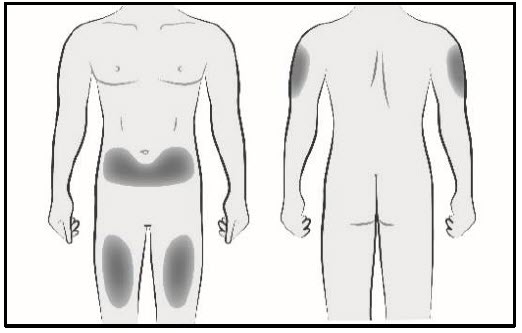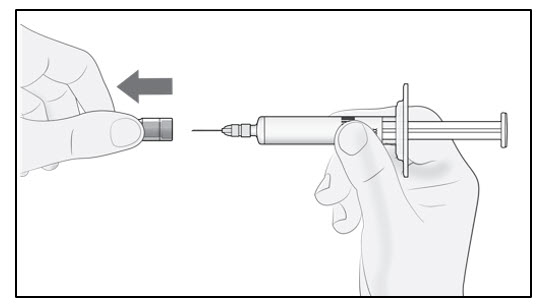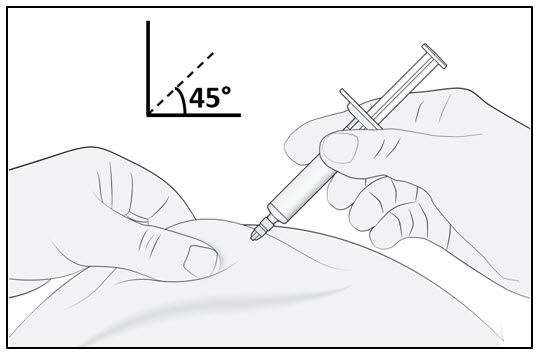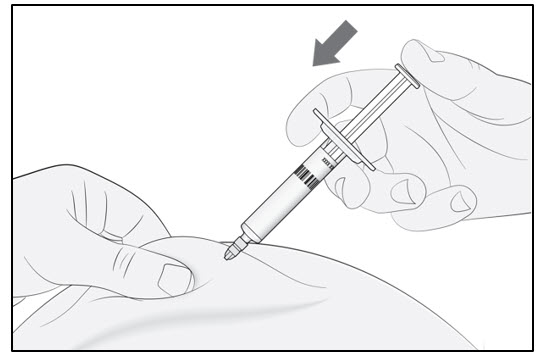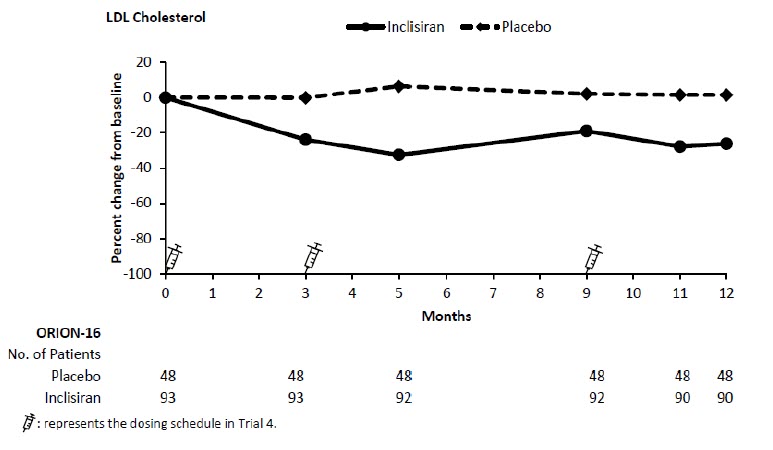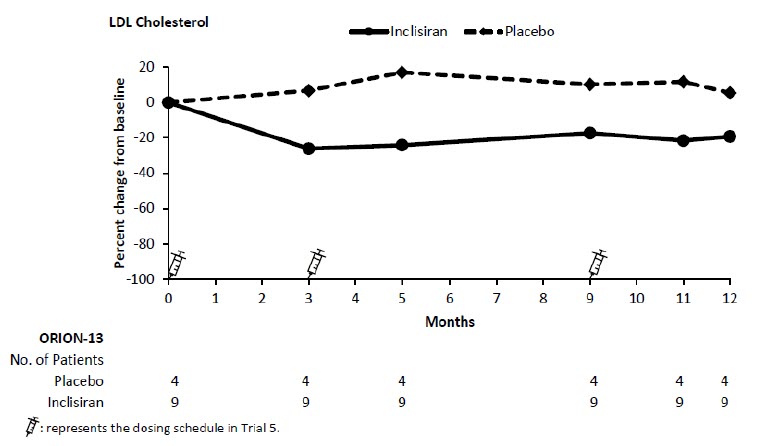 DRUG LABEL: LEQVIO
NDC: 0078-1000 | Form: INJECTION, SOLUTION
Manufacturer: Novartis Pharmaceuticals Corporation
Category: prescription | Type: HUMAN PRESCRIPTION DRUG LABEL
Date: 20260212

ACTIVE INGREDIENTS: INCLISIRAN SODIUM 284 mg/1.5 mL
INACTIVE INGREDIENTS: WATER; SODIUM HYDROXIDE; PHOSPHORIC ACID

HIGHLIGHTS OF PRESCRIBING INFORMATION

These highlights do not include all the information needed to use LEQVIO safely and effectively. See full prescribing information for LEQVIO.
LEQVIO® (inclisiran) injection, for subcutaneous use
Initial U.S. Approval: 2021

RECENT MAJOR CHANGES

Indications and Usage (1) | 07/2025, 02/2026
Contraindications (4) | 02/2026
Warnings and Precautions (5.1) | 02/2026

1 INDICATIONS AND USAGE

LEQVIO is a small interfering RNA (siRNA) directed to proprotein convertase subtilisin kexin type 9 (PCSK9) mRNA indicated as an adjunct to diet and exercise to reduce low-density lipoprotein cholesterol (LDL-C) in:

- adults with hypercholesterolemia. (1)
- adults and pediatric patients aged 12 years and older with heterozygous familial hypercholesterolemia (HeFH). (1)
- pediatric patients aged 12 years and older with homozygous familial hypercholesterolemia (HoFH). (1)

2 DOSAGE AND ADMINISTRATION

- The recommended dosage of LEQVIO for adults and pediatric patients aged 12 years and older is 284 mg administered as a single subcutaneous injection initially, again at 3 months, and then every 6 months. (2.1)
- LEQVIO should be administered by a healthcare professional. (2.2)
- Inject LEQVIO subcutaneously into the abdomen, upper arm, or thigh. (2.2)

3 DOSAGE FORMS AND STRENGTHS

Injection: 284 mg/1.5 mL (189 mg/mL) in a single-dose prefilled syringe. (3)

4 CONTRAINDICATIONS

Prior serious hypersensitivity to inclisiran or any of the excipients in LEQVIO.

5 WARNINGS AND PRECAUTIONS

Hypersensitivity Reactions: Have been reported in patients treated with LEQVIO. Advise patients on the signs and symptoms of hypersensitivity reactions and instruct patients to seek medical attention promptly. (5.1)

6 ADVERSE REACTIONS

Common adverse reactions in clinical trials (≥ 3%): injection site reaction, arthralgia, and bronchitis. (6)

To report SUSPECTED ADVERSE REACTIONS, contact Novartis Pharmaceuticals Corporation at 1-888-669-6682 or FDA at 1-800-FDA-1088 or www.fda.gov/medwatch.

FULL PRESCRIBING INFORMATION

1 INDICATIONS AND USAGE

LEQVIO® is indicated as an adjunct to diet and exercise to reduce low-density lipoprotein cholesterol (LDL-C) in:

- adults with hypercholesterolemia.
- adults and pediatric patients aged 12 years and older with heterozygous familial hypercholesterolemia (HeFH).
- pediatric patients aged 12 years and older with homozygous familial hypercholesterolemia (HoFH).

2 DOSAGE AND ADMINISTRATION

2.1 Recommended Dosage

- The recommended dosage of LEQVIO for adults and pediatric patients aged 12 years and older is 284 mg administered as a single subcutaneous injection initially, again at 3 months, and then every 6 months.
- If a planned dose is missed by less than 3 months, administer LEQVIO and maintain dosing according to the patient’s original schedule.
- If a planned dose is missed by more than 3 months, restart with a new dosing schedule - administer LEQVIO initially, again at 3 months, and then every 6 months.
- Assess LDL-C when clinically indicated. The LDL-lowering effect of LEQVIO may be measured as early as 30 days after initiation and anytime thereafter without regard to timing of the dose.

2.2 Important Administration Instructions

- LEQVIO should be administered by a healthcare professional.
- Inject LEQVIO subcutaneously into the abdomen, upper arm, or thigh. Do not inject in areas of active skin disease or injury, such as sunburns, skin rashes, inflammation, or skin infections.
- Inspect LEQVIO visually before use. It should appear clear and colorless to pale yellow. Do not use if particulate matter or discoloration is seen.

For more detailed instruction on administration of the prefilled syringe, see Instructions for Use.

3 DOSAGE FORMS AND STRENGTHS

Injection: 284 mg/1.5 mL (189 mg/mL) of inclisiran as a clear, and colorless to pale yellow solution in a single-dose prefilled syringe.

4 CONTRAINDICATIONS

LEQVIO is contraindicated in patients with a prior serious hypersensitivity reaction to inclisiran or any of the excipients in LEQVIO. Serious hypersensitivity reactions have included anaphylaxis and angioedema [see Adverse Reactions (6.2)].

5 WARNINGS AND PRECAUTIONS

5.1 Hypersensitivity Reactions

Hypersensitivity reactions, including anaphylaxis and angioedema, have been reported in patients treated with LEQVIO [see Adverse Reactions (6.2)]. Advise patients on the signs and symptoms of hypersensitivity reactions and instruct patients to seek medical attention promptly. LEQVIO is contraindicated in patients with a prior serious hypersensitivity reaction to inclisiran or any of the excipients in LEQVIO.

6 ADVERSE REACTIONS

The following adverse reactions are also discussed in other sections of the label:

- Hypersensitivity Reactions [see Warnings and Precautions (5.1)]

6.1 Clinical Trials Experience

Because clinical trials are conducted under widely varying conditions, adverse reaction rates observed in the clinical trials of a drug cannot be directly compared to rates in the clinical trials of another drug and may not reflect the rates observed in practice.

Adverse Reactions in Adults with Hypercholesterolemia

The data in Table 1 are derived from 3 placebo-controlled trials that included 1,833 adults with hypercholesterolemia treated with LEQVIO, including 1,682 exposed for 18 months (median treatment duration of 77 weeks) [see Clinical Studies (14)]. The mean age of the population was 64 years, 32% of the population were female, 92% were White, 6% were Black or African American, 1% were Asian, and < 1% were other races; 6% identified as Hispanic or Latino ethnicity. At baseline, 12% of patients had a diagnosis of HeFH and 85% had clinical atherosclerotic cardiovascular disease (ASCVD).

Adverse reactions reported in at least 3% of LEQVIO-treated patients, and more frequently than in placebo-treated patients, are shown in Table 1.

Table 1: Adverse Reactions Occurring in Greater Than or Equal to 3% of LEQVIO-treated Adults with Hypercholesterolemia and More Frequently than with Placebo (Trials 1, 2, and 3)
Adverse Reactions | Placebo (N = 1,822) % | LEQVIO (N = 1,833) %
Injection site reaction† | 2 | 8
Arthralgia | 4 | 5
Bronchitis | 3 | 4
†includes related terms such as: injection site pain, erythema and rash

Adverse reactions led to discontinuation of treatment in 2.5% of patients treated with LEQVIO and 1.9% of patients treated with placebo. The most common adverse reactions leading to treatment discontinuation in patients treated with LEQVIO were injection site reactions (0.2% versus 0% for LEQVIO and placebo, respectively).

Adverse Reactions in Pediatric Patients with HeFH

In a 24-month, two-part trial of 141 pediatric patients aged 12 years and older with HeFH (Trial 4), consisting of a 12-month randomized, double-blind, placebo-controlled part (Part 1/Year 1), followed by a 12-month open-label part (Part 2/Year 2), 93 patients received 284 mg of LEQVIO subcutaneously during Part 1 and 139 patients were treated with LEQVIO during Part 2 [see Clinical Studies (14)]. During Part 2, 91 patients continued LEQVIO treatment for a second year and 48 patients switched from placebo to LEQVIO for 1 year of treatment. The safety profile reported in pediatric patients with HeFH was consistent with the description above for adult patients with hypercholesterolemia, with the exception of headache. In pediatric patients with HeFH, the incidence of headache was 6% among patients who received placebo versus 13% of LEQVIO-treated patients during the double-blind study period.

Adverse Reactions in Pediatric Patients with HoFH

In a 24-month, two-part trial of 13 pediatric patients aged 12 years and older with HoFH (Trial 5), consisting of a 12-month randomized, double-blind, placebo-controlled part (Part 1/Year 1), followed by a 12-month open-label part (Part 2/Year 2), 9 patients received 284 mg of LEQVIO administered subcutaneously during Part 1 and 13 patients were treated with LEQVIO during Part 2 [see Clinical Studies (14)]. During Part 2, 9 patients continued LEQVIO treatment for a second year and 4 patients switched from placebo to LEQVIO for 1 year of treatment. The safety profile reported in pediatric patients was consistent with adult patients with hypercholesterolemia.

6.2 Postmarketing Experience

The following adverse reactions have been identified during post-approval use of LEQVIO. Because these reactions are reported voluntarily from a population of uncertain size, it is not always possible to reliably estimate their frequency or establish a causal relationship to drug exposure.

Hypersensitivity: anaphylaxis, angioedema, rash, pruritus, and urticaria.

8 USE IN SPECIFIC POPULATIONS

8.1 Pregnancy

Risk Summary

Discontinue LEQVIO when pregnancy is recognized. Alternatively, consider the ongoing therapeutic needs of the individual patient. Inclisiran increases LDL-C uptake and lowers LDL-C levels in the circulation, thus decreasing cholesterol and possibly other biologically active substances derived from cholesterol; therefore, LEQVIO may cause fetal harm when administered to pregnant patients based on the mechanism of action [see Clinical Pharmacology (12.1)]. In addition, treatment of hypercholesterolemia is not generally necessary during pregnancy. Atherosclerosis is a chronic process and the discontinuation of lipid-lowering drugs during pregnancy should have little impact on the outcome of long-term therapy of hypercholesterolemia for most patients.

There are no available data on the use of LEQVIO in pregnant patients to evaluate for a drug-associated risk of major birth defects, miscarriage or adverse maternal or fetal outcomes.

In animal reproduction studies, no adverse developmental effects were observed in rats and rabbits with subcutaneous administration of inclisiran during organogenesis at doses up to 5 to 10 times the maximum recommended human dose (MRHD) based on body surface area (BSA) comparison (see Data). No adverse developmental outcomes were observed in offspring of rats administered inclisiran from organogenesis through lactation at 5 times the MRHD based on BSA comparison (see Data).

The estimated background risk of major birth defects and miscarriage for the indicated population is unknown. In the U.S. general population, the estimated background risk of major birth defects and miscarriage in clinically recognized pregnancies is 2%–4% and 15%–20%, respectively.

Data

Animal Data

In embryo-fetal development studies conducted in Sprague-Dawley rats and New Zealand White rabbits, inclisiran was administered by subcutaneous injection at dose levels of 50, 100, and 150 mg/kg once daily during organogenesis (rats: Gestation Days 6 to 17; rabbits: Gestation Days 7 to 19). There was no evidence of embryo-fetal toxicity or teratogenicity at doses up to 5 and 10 times, respectively, the MRHD based on BSA comparison/dose. Inclisiran crosses the placenta and was detected in rat fetal plasma at concentrations that were 65 to 154 times lower than maternal levels.

In a pre- and postnatal development study conducted in Sprague-Dawley rats, inclisiran was administered once daily by subcutaneous injection at levels of 50, 100, and 150 mg/kg from Gestation Day 6 through Lactation Day 20. Inclisiran was well-tolerated in maternal rats, with no evidence of maternal toxicity and no effects on maternal performance. There were no effects on the development of the F1 generation, including survival, growth, physical and reflexological development, behavior, and reproductive performance at doses up to 5 times the MRHD, based on BSA comparison/dose.

8.2 Lactation

Risk Summary

There is no information on the presence of inclisiran in human milk, the effects on the breastfed infant, or the effects on milk production. Inclisiran was present in the milk of lactating rats in all dose groups. When a drug is present in animal milk, it is likely that the drug will be present in human milk (see Data). Oligonucleotide-based products typically have poor oral bioavailability; therefore, it is considered unlikely that low levels of inclisiran present in milk will adversely impact an infant’s development during lactation. The developmental and health benefits of breastfeeding should be considered along with the mother’s clinical need for LEQVIO and any potential adverse effects on the breastfed infant from LEQVIO or from the underlying maternal condition.

Data

In lactating rats, inclisiran was detected in milk at mean maternal plasma: milk ratios that ranged between 0.361 and 1.79. However, there is no evidence of systemic absorption in the suckling rat neonates.

8.4 Pediatric Use

The safety and effectiveness of LEQVIO as an adjunct to diet and other LDL-C-lowering therapies for the treatment of HeFH have been established in pediatric patients aged 12 years and older. Use of LEQVIO for this indication is based on data from a 12-month, randomized, placebo-controlled, double-blind study in 141 pediatric patients with HeFH. This indication is also supported by evidence from an adequate and well-controlled study in adults with HeFH. The safety profile reported in pediatric patients aged 12 years and older with HeFH was consistent with adult patients with hypercholesterolemia, with the exception of headache [see Adverse Reactions (6.1), Clinical Studies (14)].

The safety and effectiveness of LEQVIO as an adjunct to diet and other LDL-C-lowering therapies for the treatment of HoFH have been established in pediatric patients aged 12 years and older. Use of LEQVIO for this indication is based on data from a 12-month, randomized, placebo-controlled, double-blind study in 13 pediatric patients with HoFH [see Adverse Reactions (6.1), Clinical Studies (14)].

The safety and effectiveness of LEQVIO have not been established in pediatric patients with HeFH or HoFH younger than 12 years of age. The safety and effectiveness of LEQVIO has not been established in pediatric patients with other types of hypercholesterolemia.

8.5 Geriatric Use

Of the 1,833 patients treated with LEQVIO in clinical trials, 981 (54%) patients were 65 years of age and older, while 239 (13%) patients were 75 years of age and older. No overall differences in safety or effectiveness were observed between patients 65 years of age and older and younger adult patients.

8.6 Renal Impairment

No dose adjustments are necessary for patients with mild, moderate, or severe renal impairment [see Clinical Pharmacology (12.3)]. LEQVIO has not been studied in patients with end stage renal disease [see Clinical Pharmacology (12.3)].

8.7 Hepatic Impairment

No dose adjustment is necessary in patients with mild to moderate hepatic impairment. LEQVIO has not been studied in patients with severe hepatic impairment [see Clinical Pharmacology (12.3)].

11 DESCRIPTION

LEQVIO contains inclisiran sodium, a small interfering RNA (siRNA) directed to proprotein convertase subtilisin kexin type 9 (PCSK9) mRNA. Inclisiran contains a covalently linked ligand containing three N-acetylgalactosamine (GalNAc) residues to facilitate delivery to hepatocytes. With one exception, the 2'ribose moieties of the inclisiran sodium are present as 2'-F or 2'-OMe ribonucleotide. In addition, six of the terminal phosphodiester backbones are present as phosphorothioate linkages as indicated below.

The molecular formula of inclisiran sodium is C529H664F12N176Na43O316P43S6 and its molecular weight is 17,284.72 g/mol. It has the following structural formula:

Abbreviations: Af = adenine 2'-F ribonucleotide; Cf = cytosine 2'-F ribonucleotide; Gf = guanine 2'-F ribonucleotide; Am = adenine 2'-OMe ribonucleotide; Cm = cytosine 2'-OMe ribonucleotide; Gm = guanine 2'-OMe ribonucleotide; Um = uracil 2'-OMe ribonucleotide; L96 = triantennary GalNAc (N-acetyl-galactosamine)

LEQVIO is a sterile, preservative-free, clear, and colorless to pale yellow solution for subcutaneous use in a prefilled syringe. Each syringe contains 1.5 mL of solution containing the equivalent of 284 mg inclisiran (present as 300 mg inclisiran sodium salt). LEQVIO is formulated in Water for Injection and may also contain sodium hydroxide and/or phosphoric acid for pH adjustment to a target pH of 7.0.

12 CLINICAL PHARMACOLOGY

12.1 Mechanism of Action

Inclisiran is a double-stranded small interfering ribonucleic acid (siRNA), conjugated on the sense strand with triantennary N-Acetylgalactosamine (GalNAc) to facilitate uptake by hepatocytes. In hepatocytes, inclisiran utilizes the RNA interference mechanism and directs catalytic breakdown of mRNA for PCSK9. This increases LDL-C receptor recycling and expression on the hepatocyte cell surface, which increases LDL-C uptake and lowers LDL-C levels in the circulation.

12.2 Pharmacodynamics

Following a single subcutaneous administration of 284 mg of inclisiran, LDL-C reduction was apparent within 14 days post dose. Mean reductions of 38% to 51% for LDL-C were observed 30 to 180 days post dose. At Day 180, LDL-C levels were still reduced by approximately 53%.

Following a dose at Day 1 and Day 90 of 284 mg of inclisiran, mean serum PCSK9 levels were reduced by approximately 75% and 69% at Day 120, and Day 180, respectively.

In the clinical trials, following four doses of LEQVIO at Day 1, Day 90 (3 months), Day 270 (~6 months) and Day 450 (~12 months), LDL-C, total cholesterol, ApoB, and non-HDL-C were reduced [see Clinical Studies (14)].

Cardiac Electrophysiology

At a dose 3 times the maximum recommended dose, inclisiran does not prolong the QT interval to any clinically relevant extent.

12.3 Pharmacokinetics

Absorption

Following a single subcutaneous administration, systemic exposure to inclisiran increased in a linear and dose proportional manner over a range from 25 mg to 800 mg of inclisiran sodium. At the recommended dosing regimen of 284 mg of LEQVIO, plasma concentrations reached peak in approximately 4 hours post dose with a mean Cmax of 509 ng/mL. Concentrations reached undetectable levels after 24 to 48 hours post dosing. The mean area under the plasma concentration-time curve from dosing extrapolated to infinity was 7,980 ng*h/mL. Pharmacokinetic findings following multiple subcutaneous administrations of LEQVIO were similar to single-dose administration.

Distribution

Inclisiran is 87% protein bound in vitro at the relevant clinical plasma concentrations. Following a single subcutaneous 284 mg dose of LEQVIO to healthy adults, the apparent volume of distribution is approximately 500 L. Inclisiran has been shown to have high uptake into, and selectively for the liver, the target organ for cholesterol lowering.

Elimination

The terminal elimination half-life of LEQVIO is approximately 9 hours, and no accumulation occurs with multiple dosing.

Metabolism

Inclisiran is primarily metabolized by nucleases to shorter nucleotides of varying length. Inclisiran is not a substrate for CYP450 or transporters.

Excretion

Approximately 16% of LEQVIO is cleared through the kidney.

Specific Populations

Male and Female Patients and Racial or Ethnic Groups

A population pharmacodynamic analysis was conducted on data from 4,328 patients. Age, body weight, gender, race, and creatinine clearance were found not to significantly influence inclisiran pharmacokinetics.

Pediatric Patients

The pharmacokinetics of LEQVIO were evaluated in pediatric patients aged 12 years and older with HeFH (Trial 4) or HoFH (Trial 5) [see Use in Specific Populations (8.4), Clinical Studies (14)]. Inclisiran plasma concentrations in pediatric patients at the clinically recommended dose were similar to adults.

Patients with Renal Impairment

Pharmacokinetic analysis of data from a dedicated renal impairment study reported increases in inclisiran Cmax and AUC of approximately 2.3 to 3.3-fold and 1.6 to 2.3-fold, respectively, in patients with mild, moderate or severe renal impairment, relative to patients with normal renal function. Despite the higher plasma exposures, reductions in LDL-C were similar across all groups based on renal function.

Patients with Hepatic Impairment

Pharmacokinetic analysis of data from a dedicated hepatic impairment study reported increases in inclisiran Cmax and AUC of approximately 1.1- to 2.1-fold and 1.3- to 2.0-fold, respectively, in patients with mild and moderate hepatic impairment, relative to patients with normal hepatic function. Despite the higher plasma inclisiran exposures, reductions in LDL-C were similar between the groups of patients administered inclisiran with normal hepatic function and mild hepatic impairment. In patients with moderate hepatic impairment, baseline PCSK9 levels were lower and reductions in LDL-C were less than those observed in patients with normal hepatic function. LEQVIO has not been studied in patients with severe hepatic impairment.

Drug Interaction Studies

No formal clinical drug interaction studies have been performed. The components of LEQVIO are not substrates, inhibitors or inducers of cytochrome P450 enzymes or transporters. In a population pharmacokinetic analysis, concomitant use of inclisiran did not have a clinically significant impact on atorvastatin or rosuvastatin concentrations. LEQVIO is not expected to cause drug-drug interactions or to be affected by inhibitors or inducers of cytochrome P450 enzymes or transporters.

12.6 Immunogenicity

The observed incidence of anti-drug antibodies (ADA) is highly dependent on the sensitivity and specificity of the assay. Differences in assay methods preclude meaningful comparisons of the incidence of ADA in the studies described below with the incidence of ADA in other studies, including those of inclisiran.

The immunogenicity of LEQVIO has been evaluated using screening and confirmatory immunoassays for the detection of binding anti-inclisiran antibodies.

Samples from 1,830 adult patients in the placebo-controlled clinical trials were tested for ADA [see Clinical Studies (14)]. Confirmed positivity was detected in 33/1,830 (2%) patients prior to receiving LEQVIO and in 90/1,830 (5%) patients during the 18 months of treatment with LEQVIO. Approximately 31/1,830 (2%) LEQVIO-treated adult patients with a negative sample at baseline had a persistent anti-inclisiran antibody response, defined as two confirmed positive samples separated by at least 16 weeks or a single confirmed positive final sample.

In pediatric patients with HeFH, confirmed positivity was not detected in Year 1 (12 months of double-blind period), but was detected in 8/139 (6%) patients in Year 2 (12 months of open-label period). In pediatric patients with HoFH, confirmed positivity was detected in 1/13 (8%) patient at pre-dose and throughout the trial (12 months of double-blind period and 12 months of open-label period) [see Clinical Studies (14)].

There was no identified clinically significant effect of anti-inclisiran antibodies on pharmacodynamics, safety, or effectiveness of LEQVIO in adults and pediatrics during the placebo-controlled studies. However, the long-term consequences of continuing LEQVIO treatment in the presence of anti-inclisiran binding antibodies are unknown.

13 NONCLINICAL TOXICOLOGY

13.1 Carcinogenesis, Mutagenesis, Impairment of Fertility

In a 2-year carcinogenicity study, Sprague-Dawley rats were administered subcutaneous doses of 40, 95, or 250 mg/kg inclisiran once every 28 days (1, 3, or 8 times the MRHD, based on BSA comparison/dose). Inclisiran was not carcinogenic up to the highest dose tested.

In a 26-week study in RasH2Tg mice, subcutaneous doses of 300, 600, or 1,500 mg/kg once every 28 days were administered. Inclisiran was not carcinogenic up to the highest dose tested.

Inclisiran was not mutagenic or clastogenic in a standard battery of genotoxicity tests, including a bacterial mutagenicity assay, an in vitro chromosome aberration assay using human peripheral lymphocytes, and an in vivo bone marrow micronucleus assay in rats.

Fertility and early embryonic-development studies were conducted in male and female rats. In male rats, inclisiran was administered subcutaneously at dose levels of 10, 50, and 250 mg/kg every 2 weeks for 4 weeks before cohabitation through mating, and until termination between Days 64 and 67. In female rats, inclisiran was administered subcutaneously at dose levels of 10, 50, and 250 mg/kg once every 4 days beginning 14 days prior to cohabitation and through mating, followed by 10, 50, or 150 mg/kg once daily during the gestation period up to Gestation Day 7. There were no adverse effects on fertility up to the highest dose examined, corresponding to 8 times the MRHD, based on BSA comparison/dose.

14 CLINICAL STUDIES

Adults with Primary Hypercholesterolemia or HeFH

The efficacy of LEQVIO was investigated in three randomized, double-blind, placebo-controlled trials that enrolled 3,660 adults with HeFH, clinical ASCVD, or increased risk for ASCVD, who were taking maximally tolerated statin therapy and who required additional LDL-C lowering. Demographics and baseline disease characteristics were balanced between the treatment arms in all trials.

Adults with Primary Hypercholesterolemia

Trial 1 (ORION-10, NCT03399370) was a multicenter, double-blind, randomized, placebo-controlled 18-month trial in which 1,561 adults with ASCVD were randomized 1:1 to receive subcutaneous injections of either LEQVIO 284 mg (n = 781) or placebo (n = 780) on Day 1, Day 90, Day 270, and at Day 450. Patients were taking a maximally tolerated dose of statin with or without other lipid modifying therapy and required additional LDL-C reduction. Patients were stratified by current use of statins or other lipid-modifying therapies. Patients taking PCSK9 inhibitors were excluded from the trial.

The mean age at baseline was 66 years (range: 35 to 90 years), 60% were ≥65 years old, 31% were female, 86% were White, 13% were Black or African American, 1% were Asian, and 14% identified as Hispanic or Latino ethnicity. Forty-five percent (45%) of patients had diabetes at baseline. The mean baseline LDL-C was 105 mg/dL. At the time of randomization, 89% of patients were receiving statin therapy and 69% were receiving high-intensity statin therapy.

The primary efficacy outcome measure in Trial 1 was the percent change from baseline to Day 510 in LDL-C. The difference between the LEQVIO and placebo groups in mean percentage change in LDL-C from baseline to Day 510 was -52% (95% CI: -56%, -49%; p < 0.0001). For additional results, see Table 2 and Figure 1.

Table 2: Changes in Lipid Parameters in Adults with Hypercholesterolemia and ASCVD on Maximally Tolerated Statin Therapy (Mean % Change from Baseline to Day 510 in Trial 1)
Treatment Group | LDL-C | Total Cholesterol | Non-HDL-C | ApoB
Day 510 (mean percentage change from baseline)a
Placebo (n = 780) | 1 | 0 | 0 | -2
LEQVIO (n = 781) | -51 | -34 | -47 | -45
Difference from placebo (LS Mean) (95% CI) | -52 (-56, -49) | -33 (-35, -31) | -47 (-50, -44) | -43 (-46, -41)
ApoB = apolipoprotein B; CI = confidence interval; HDL-C = high-density lipoprotein cholesterol; LDL-C = low-density lipoprotein cholesterol
a11.5% of subjects on LEQVIO and 14.6% of subjects on placebo had missing LDL-C data at primary endpoint (Day 510). Missing data were imputed using a modified control-based multiple imputation to account for treatment adherence. Percent change from baseline in LDL-C was analyzed using analysis of covariance (ANCOVA) with fixed effect for treatment group and baseline LDL-C as a covariate. Other endpoints were analyzed using a mixed-effect model for repeated measure (MMRM) with fixed effects for treatment group, visit, interaction between treatment and visit, and baseline value. Missing data were imputed using a control-based pattern-mixture model approach.

Figure 1: Mean Percent Change from Baseline in LDL-C Over 18 Months in Adults with Hypercholesterolemia and ASCVD on Maximally Tolerated Statin Therapy (Trial 1)

Trial 2 (ORION-11, NCT03400800) was a multicenter, double-blind, randomized, placebo-controlled 18-month trial in which 1,617 adults with ASCVD or increased risk for ASCVD were randomized 1:1 to receive subcutaneous injections of either LEQVIO 284 mg (n = 810) or placebo (n = 807) on Day 1, Day 90, Day 270, and Day 450. Patients were taking a maximally tolerated dose of statin with or without other lipid modifying therapy and required additional LDL-C reduction. Patients were stratified by country and by current use of statins or other lipid-modifying therapies. Patients taking PCSK9 inhibitors were excluded from the trial.

The mean age at baseline was 65 years (range: 20 to 88 years), 55% were ≥65 years old, 28% were female, 98% were White, 1% were Black or African American, and <1% were Asian; <1% identified as Hispanic or Latino ethnicity. Thirty-five percent (35%) of patients had diabetes at baseline. The mean baseline LDL-C was 105 mg/dL. At the time of randomization, 95% of patients were receiving statin therapy and 78% were receiving high-intensity statin therapy.

The primary efficacy outcome measure in Trial 2 was the percent change from baseline to Day 510 in LDL-C. The difference between the LEQVIO and placebo groups in mean percentage change in LDL-C from baseline to Day 510 was -50% (95% CI: -53%, -47%; p < 0.0001). For additional results, see Table 3 and Figure 2.

Table 3: Changes in Lipid Parameters in Adults with Hypercholesterolemia and ASCVD or Increased Risk for ASCVD on Maximally Tolerated Statin Therapy (Mean % Change from Baseline to Day 510 in Trial 2)
Treatment Group | LDL-C | Total Cholesterol | Non-HDL-C | ApoB
Day 510 (mean percentage change from baseline)a
Placebo (n = 807) | 4 | 2 | 2 | 1
LEQVIO (n = 810) | -46 | -28 | -41 | -38
Difference from placebo (LS Mean) (95% CI) | -50 (-53, -47) | -30 (-32, -28) | -43 (-46, -41) | -39 (-41, -37)
ApoB = apolipoprotein B; CI = confidence interval; HDL-C = high-density lipoprotein cholesterol; LDL-C = low-density lipoprotein cholesterol
a10.6% of subjects on LEQVIO and 8.4% of subjects on placebo had missing LDL-C data at primary endpoint (Day 510). Missing data were imputed using a modified control-based multiple imputation to account for treatment adherence. Percent change from baseline in LDL-C was analyzed using analysis of covariance (ANCOVA) with fixed effect for treatment group and baseline LDL-C as a covariate. Other endpoints were analyzed using mixed-effect model for repeated measure (MMRM) with fixed effects for treatment group, visit, interaction between treatment and visit, and baseline value. Missing data were imputed using a control-based pattern-mixture model approach.

Figure 2: Mean Percent Change from Baseline in LDL-C Over 18 Months in Adults with Hypercholesterolemia and ASCVD or Increased Risk for ASCVD on Maximally Tolerated Statin Therapy (Trial 2)

In a pooled analysis of Trial 1 and Trial 2, the observed treatment effect was similar across predefined subgroups, such as sex, age, race, disease characteristics, geographic regions, presence of diabetes, body mass index, baseline LDL-C levels, and intensity of statin treatment.

Adults with HeFH

Trial 3 (ORION-9, NCT03397121) was a multicenter, double-blind, randomized, placebo-controlled 18-month trial in which 482 adults with HeFH were randomized 1:1 to receive subcutaneous injections of either LEQVIO 284 mg (n = 242) or placebo (n = 240) on Day 1, Day 90, Day 270, and at Day 450. Patients with HeFH were taking a maximally tolerated dose of statin with or without other lipid modifying therapy and required additional LDL-C reduction. The diagnosis of HeFH was made either by genotyping or clinical criteria using either the Simon Broome or WHO/Dutch Lipid Network criteria. Patients were stratified by country and by current use of statins or other lipid-modifying therapies. Patients taking PCSK9 inhibitors were excluded from the trial.

The mean age at baseline was 55 years (range: 21 to 80 years), 22% were ≥65 years old, 53% were female, 94% were White, 3% were Black or African American, and 3% were Asian; and 3% identified as Hispanic or Latino ethnicity. Ten percent (10%) of patients had diabetes at baseline. The mean baseline LDL-C was 153 mg/dL. At the time of randomization, 90% of patients were receiving statin therapy and 74% were receiving high-intensity statin therapy. Fifty-two percent (52%) of patients were treated with ezetimibe. The most commonly administered statins were atorvastatin and rosuvastatin.

The primary efficacy outcome measure in Trial 3 was the percent change from baseline to Day 510 in LDL-C. The difference between the LEQVIO and placebo groups in mean percentage change in LDL-C from baseline to Day 510 was -48% (95% CI: -54%, -42%; p < 0.0001). For additional results, see Table 4 and Figure 3.

Table 4: Changes in Lipid Parameters in Adults with HeFH on Maximally Tolerated Statin Therapy (Mean % Change from Baseline to Day 510 in Trial 3)
Treatment Group | LDL-C | Total Cholesterol | Non-HDL-C | ApoB
Day 510 (mean percentage change from baseline)a
Placebo (n = 240) | 8 | 7 | 7 | 3
LEQVIO (n = 242) | -40 | -25 | -35 | -33
Difference from placebo (LS Mean) (95% CI) | -48 (-54, -42) | -32 (-36, -28) | -42 (-47, -37) | -36 (-40, -32)
ApoB = apolipoprotein B; CI = confidence interval; HDL-C = high-density lipoprotein cholesterol; LDL-C = low-density lipoprotein cholesterol
a4.5% of subjects on LEQVIO and 4.6% of subjects on placebo had missing LDL-C data at primary endpoint (Day 510). Missing data were imputed using a modified control-based multiple imputation to account for treatment adherence. Percent change from baseline in LDL-C was analyzed using analysis of covariance (ANCOVA) with fixed effect for treatment group and baseline LDL-C as a covariate. Other endpoints were analyzed using mixed-effect model for repeated measure (MMRM) with fixed effects for treatment group, visit, interaction between treatment and visit, and baseline value as a covariate. Missing data were imputed using a control-based pattern-mixture model approach.

Figure 3: Mean Percent Change from Baseline in LDL-C Over 18 Months in Adults with HeFH on Maximally Tolerated Statin Therapy (Trial 3)

Pediatric Patients with HeFH

Trial 4 (ORION-16, NCT04652726) was a 12-month randomized, double-blind, placebo-controlled trial in 141 pediatric patients aged 12 years and older with HeFH and elevated LDL-C. Patients were receiving maximally tolerated statin therapy with or without additional LDL-C-lowering therapies. The diagnosis of HeFH was made either by genetic testing or clinical criteria. Patients were randomized in a 2:1 ratio to receive subcutaneous injections of either LEQVIO 284 mg (n = 93) or placebo (n = 48) on Day 1, Day 90, and Day 270.

The mean age at baseline was 15 years (range: 12 to 17 years), 53% were female, 91% were White, 4% were Black or African American, 3% were Asian, and 3% were other races; 9% identified as Hispanic or Latino ethnicity. The mean LDL-C at baseline was 183 mg/dL; 93% of patients were taking statins and 23% were on ezetimibe.

The primary efficacy outcome measure in Trial 4 was the percent change from baseline to Day 330 in LDL-C. The difference between the LEQVIO and placebo groups in mean percentage change in LDL-C from baseline to Day 330 was -29% (95% CI: −36%, −21%; p < 0.0001). For additional results, see Table 5 and Figure 4.

Table 5: Changes in Lipid Parameters in Pediatric Patients aged 12 Years and Older with HeFH (Mean % Change from Baseline to Day 330 in Trial 4)
Treatment Group | LDL-C | ApoB | Non-HDL-C | Total Cholesterol
Day 330 (mean percentage change from baseline)a
Placebo (n = 48) | 1 | 4 | 2 | 0
LEQVIO (n = 93) | -27 | -21 | -25 | -19
Difference from placebo (LS Mean) (95% CI) | -29 (-36, -21) | -26 (-32, -20) | -27 (-34, -20) | -19 (-25, -14)
ApoB = apolipoprotein B; CI = confidence interval; HDL-C = high-density lipoprotein cholesterol; LDL-C = low-density lipoprotein cholesterol
a3.2% of subjects on LEQVIO and 0% of subjects on placebo had missing LDL-C data at primary endpoint (Day 330). Missing data were imputed using a modified control-based multiple imputation to account for treatment adherence. Percent change from baseline in LDL-C was analyzed using analysis of covariance (ANCOVA) with fixed effects for treatment group and baseline age group, and baseline LDL-C as a covariate. Other endpoints were analyzed using same approach.

Figure 4: Mean Percent Change from Baseline in LDL-C Over 12 Months in Pediatric Patients aged 12 Years and Older with HeFH (Trial 4)

Pediatric Patients with HoFH

Trial 5 (ORION-13, NCT04659863) was a 12-month randomized, double-blind, placebo-controlled trial in 13 pediatric patients aged 12 years and older with HoFH and elevated LDL-C. All patients were taking LDL-C-lowering therapies. Patients with a null (negative) variant in both low-density lipoprotein receptor (LDLR) alleles, who were considered unlikely to benefit from a reduction in PCSK9, were excluded. The diagnosis of HoFH was made by genetic testing. Patients were randomized in a 2:1 ratio to receive subcutaneous injections of either LEQVIO 284 mg (n = 9) or placebo (n = 4) on Day 1, Day 90, and Day 270.

The mean age at baseline was 15 years (range: 12 to 17 years), 69% were female, 85% were White, and 15% were Asian; 8% identified as Hispanic or Latino ethnicity. The mean LDL-C at baseline was 272 mg/dL; all patients were taking statins and 85% were on ezetimibe.

The primary efficacy outcome measure in Trial 5 was the percent change from baseline to Day 330 in LDL-C. The difference between the LEQVIO and placebo groups in mean percentage change in LDL-C from baseline to Day 330 was -33% (95% CI: −80%, 13%). For additional results, see Table 6 and Figure 5.

Table 6: Changes in Lipid Parameters in Pediatric Patients aged 12 Years and Older with HoFH (Mean % Change from Baseline to Day 330 in Trial 5)
Treatment Group | LDL-C | ApoB | Non-HDL-C | Total Cholesterol
Day 330 (mean percentage change from baseline)a
Placebo (n = 4) | 12 | 5 | 9 | 9
LEQVIO (n = 9) | -22 | -19 | -23 | -19
Difference from placebo (Mean) (95% CI) | -33 (-80, 13) | -23 (-50, 4) | -33 (-87, 22) | -28 (-75, 19)
ApoB = apolipoprotein B; CI = confidence interval; HDL-C = high-density lipoprotein cholesterol; LDL-C = low-density lipoprotein cholesterol
The trial was designed as a descriptive trial and was not powered to test any hypothesis.
aNo subject in either LEQVIO or placebo had missing LDL-C data at primary endpoint (Day 330). No statistical model was performed. The mean and 95% CI of the difference from placebo were calculated based on a t-distribution for the percent change from baseline in LDL-C and other endpoints.

Figure 5: Mean Percent Change from Baseline in LDL-C Over 12 Months in Pediatric Patients aged 12 Years and Older with HoFH (Trial 5)

16 HOW SUPPLIED/STORAGE AND HANDLING

LEQVIO injection is a clear, colorless to pale yellow solution, 284 mg/1.5 mL (189 mg/mL) of inclisiran supplied as:

Carton containing 1 single-dose prefilled syringe:

NDC 0078-1000-60

Store LEQVIO at controlled room temperature 20°C to 25°C (68°F to 77°F) with allowable excursions between 15°C and 30°C (59°F and 86°F) [see USP, Controlled Room Temperature (CRT)].

17 PATIENT COUNSELING INFORMATION

Pregnancy

Advise pregnant patients and patients who can become pregnant of the potential risk to a fetus. Advise patients to inform their healthcare provider of a known or suspected pregnancy to discuss if LEQVIO should be discontinued [see Use in Specific Populations (8.1)].

Hypersensitivity

Inform patients that serious hypersensitivity reactions, including anaphylaxis and angioedema, have been reported in patients treated with LEQVIO. Advise patients on the signs and symptoms of hypersensitivity reactions and instruct them to seek medical advice promptly if such symptoms occur [see Warnings and Precautions (5.1)].

Injection Site Reactions

Advise patients that injection site reactions can occur with LEQVIO [see Adverse Reactions (6.1)].

Distributed by:
Novartis Pharmaceuticals Corporation
East Hanover, New Jersey 07936

For more information, visit www.leqvio.com or call 1-833-LEQVIO2 (1-833-537-8462).

© Novartis

T2026-02

INSTRUCTIONS FOR USE
LEQVIO® [leck' vee oh]
(inclisiran)
injection, for subcutaneous use
284 mg/1.5 mL single-dose Prefilled Syringe

The following information is intended for healthcare professionals only.
This Instructions for Use contains information on how to inject LEQVIO using the prefilled syringe.

Important Information You Need to Know Before Injecting LEQVIO:

- Do not use the prefilled syringe if any of the seals on the outer carton or the seal of the plastic tray are broken.
- Do not remove the needle cap until you are ready to inject.
- Do not use if the prefilled syringe has been dropped after removing the needle cap.
- Do not try to re-use or take apart the prefilled syringe.

Step 1. Inspect the prefilled syringe
It should appear clear and colorless to pale yellow. Do not use if particulate matter or discoloration is seen. You may see air bubbles in the liquid, which is normal. Do not try to remove the air.

- Do not use the prefilled syringe if it looks damaged or if any of the solution for injection has leaked out of the prefilled syringe.
- Do not use the prefilled syringe after the expiration date (EXP), which is printed on the prefilled syringe label and carton.

Step 2. Select and prepare the injection site

- Choose an injection site in the abdomen, upper arm, or thigh (see Figure A). Do not inject in areas of active skin disease or injury, such as sunburns, skin rashes, inflammation, or skin infection.
- Wipe the skin with an alcohol swab. Let the injection site dry before you inject the dose.

Figure A

Step 3. Remove needle cap
Firmly pull straight to remove the needle cap from the prefilled syringe (see Figure B). You may see a drop of liquid at the end of the needle. This is normal.
Do not put the needle cap back on. Throw it away.
Note: Do not remove the needle cap until you are ready to inject. Early removal of the needle cap prior to injection can lead to drying of the drug product within the needle, which can result in needle clogging.

Figure B

Step 4. Insert the needle
Gently pinch the skin at the injection site and hold the pinch throughout the injection. With the other hand insert the needle into the skin at an angle of approximately 45 degrees as shown (see Figure C).

Figure C

Step 5. Inject
Continue to pinch the skin. Slowly press the plunger as far as it will go (see Figure D). This will make sure that a full dose is injected.
Note: If you cannot depress the plunger following insertion of the needle, use a new prefilled syringe.

Figure D

Step 6. Complete injection and dispose of the prefilled syringe
Remove the prefilled syringe from the injection site. Do not put the needle cap back on.
Dispose of the prefilled syringe in an FDA-cleared sharps disposal container right away after use.

For more information, visit www.leqvio.com or call 1-833-LEQVIO2 (1-833-537-8462).

Distributed by:
Novartis Pharmaceuticals Corporation
East Hanover, New Jersey 07936

© Novartis

This Instructions for Use has been approved by the U.S. Food and Drug Administration.

Revised: February 2026

T2026-03

PRINCIPAL DISPLAY PANEL

LEQVIO®

(inclisiran) injection

Contains One Single-dose Prefilled Syringe

For subcutaneous use

For administration by a healthcare professional only

284 mg/1.5 mL

(189 mg/mL)

NDC 0078-1000-60

Sterile Solution

Rx only

NOVARTIS